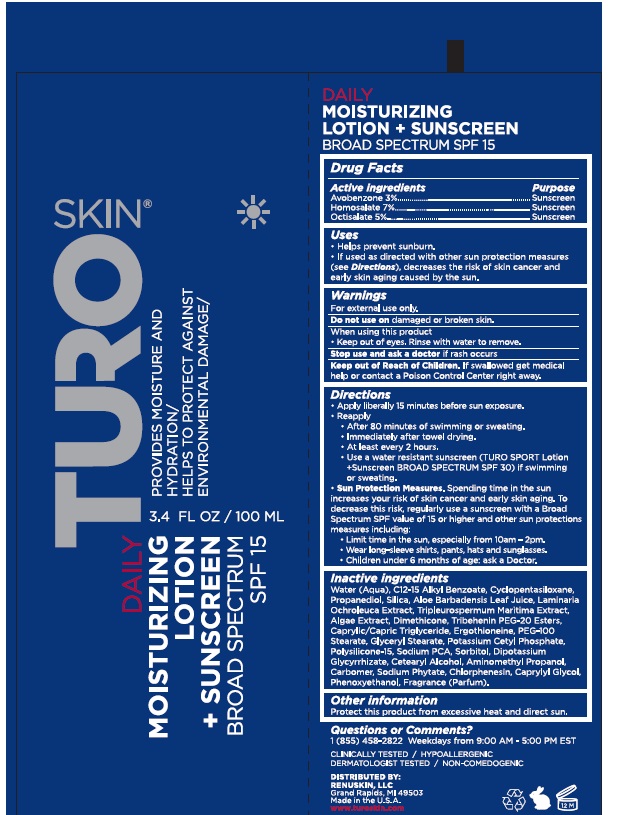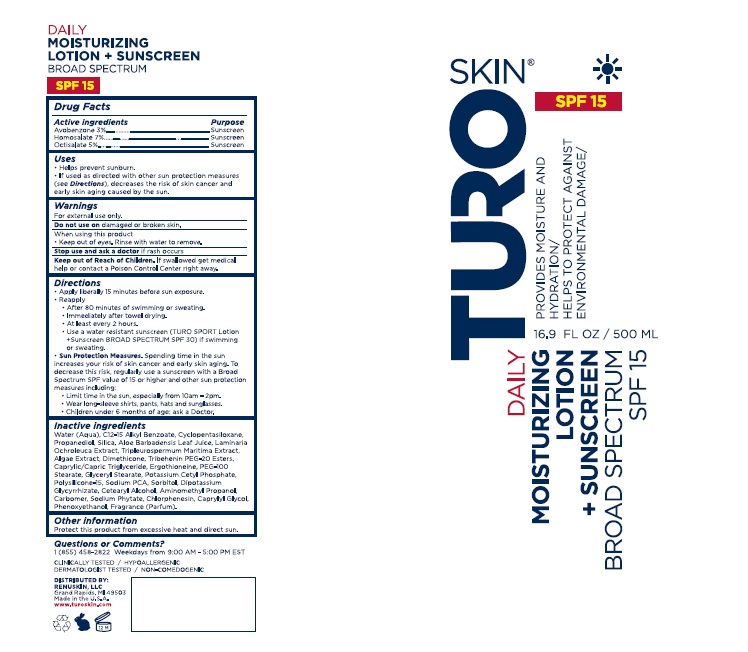 DRUG LABEL: TuroSkin Daily Moisturizing Sunscreen broadspectrum spf15
NDC: 84309-001 | Form: LOTION
Manufacturer: Renuskin LLC
Category: otc | Type: HUMAN OTC DRUG LABEL
Date: 20251112

ACTIVE INGREDIENTS: AVOBENZONE 3 g/100 mL; HOMOSALATE 7 g/100 mL; OCTISALATE 5 g/100 mL
INACTIVE INGREDIENTS: WATER; ALKYL (C12-15) BENZOATE; CYCLOMETHICONE 5; PROPANEDIOL; SILICON DIOXIDE; ALOE VERA LEAF; LAMINARIA OCHROLEUCA; TRIPLEUROSPERMUM INODORUM WHOLE; PHYMATOLITHON CALCAREUM; DIMETHICONE; TRIBEHENIN PEG-20 ESTERS; MEDIUM-CHAIN TRIGLYCERIDES; ERGOTHIONEINE; PEG-100 STEARATE; GLYCERYL MONOSTEARATE; POTASSIUM CETYL PHOSPHATE; POLYSILICONE-15; SODIUM PYRROLIDONE CARBOXYLATE; SORBITOL; GLYCYRRHIZINATE DIPOTASSIUM; CETOSTEARYL ALCOHOL; AMINOMETHYLPROPANOL; CARBOMER HOMOPOLYMER, UNSPECIFIED TYPE; PHYTATE SODIUM; CHLORPHENESIN; CAPRYLYL GLYCOL; PHENOXYETHANOL

Active ingredients Purpose

Avobenzone 3% Sunscreen

Homosalate 7% Sunscreen

Octisalate 5% Sunscreen

Uses

- Helps prevent sunburn
- If used as directed with other sun protection measures (see Direction), decreases the risk of skin cancer and early aging caused by the sun.

Warning

- For external use only.
- Do not use on damaged or broken skin.
- When using this product keep out of eyes, rinse with water to remove.
- Stop use and ask a doctor if rash occurs
- Keep out of reach of children . If swallowed get medical help or contact a Poison Control Center right away.

Directions

- Apply liberally 15 minutes before sun exposure.
- Reapply
- After 80 minutes of swimming or sweating.
- Immediately after towel drying.
- At least every 2 hours.
- Use a water resistant sunscreen (TURO SPORT Lotion + Sunscreen BROAD SPECTRUM SPF 30) if swimming or sweating.
- Sun Protection Measures.Spending time in the sun increases your risk of skin cancer and early skin aging. To decrease the risk, regularly use a sunscreen with a board spectrum SPF value of 15 or higher and other sun protection measures including:
- Limit time in the sun, especially from 10am - 2pm.
- Wear long-sleeve shirts, pants, hats and sunglasses.
- Children under 6 months of age : ask a doctor

Inactive ingredients

Water, C12-C15 Alkyl Benzoate, Cyclopentasiloxane, Propanediol, Silica, Aloe Barbadensis leaf juice, laminaria ochroleuca extract, Tripleurospermum maritima extract, Algae extract, Dimethicone, Tribehenin PEG-20 esters, caprylic / Capric Triglyceride, ergothioneeine, PEG-100 stearate, glyceryl stearate, potassium cetyl phosphate, Polysilicone-15, Sodium PCA, Sorbitol, Dipotassium glycyrrhizate, Cetearyl alcohol, Aminomethyl Propanol, Carbomer, Sodium phytate, Chlorphenesin, Caprylyl glycol, Phenoxyethanol, Fragrance (Parfum)

Other information

Protect this product from excessive heat and direct sun